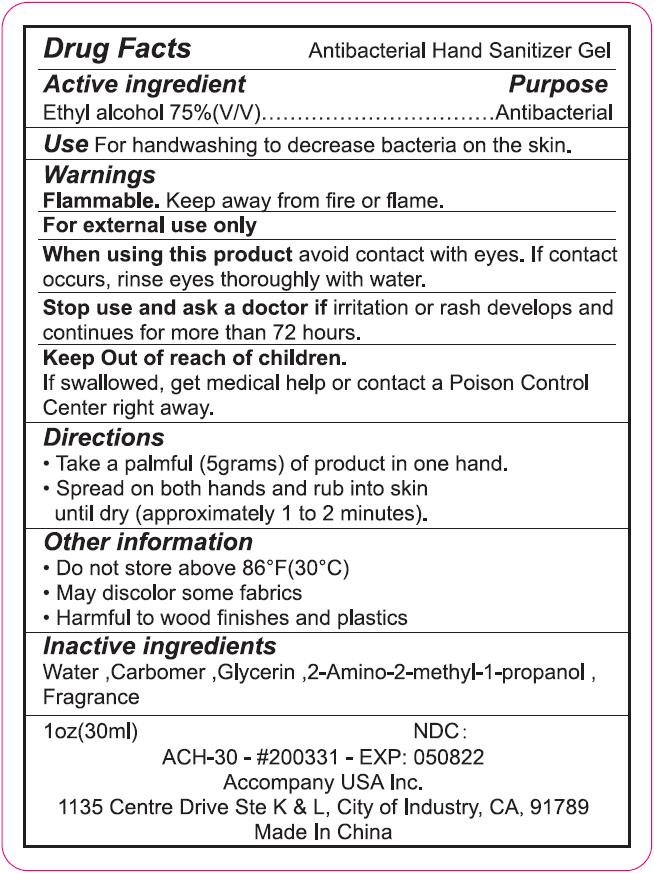 DRUG LABEL: Antibacterial Hand Sanitizer
NDC: 76816-111 | Form: GEL
Manufacturer: Accompany USA Inc
Category: otc | Type: HUMAN OTC DRUG LABEL
Date: 20200527

ACTIVE INGREDIENTS: ALCOHOL 22.5 mL/30 mL
INACTIVE INGREDIENTS: GLYCERIN; WATER; CARBOMER HOMOPOLYMER, UNSPECIFIED TYPE; LEMON OIL; AMINOMETHYLPROPANOL

Accompany, Hand Sanitizer, Gel, Alcohol 75%; 30mL

Active Ingredient(s)

Ethyl alcohol 75% v/v. Purpose: Antimicrobial

Purpose

Antibacterial

Use

For handwashing to decrease bacteria on the skin.

Warnings

Flammable. Keep away from fire or flame.

Do not use

For external use only.

When using this product avoid contact with eyes.

If contact occurs, rinse eyes thoroughly with water.

Stop use and ask a doctor if irritation or rash develops and continues for 72 hours.

Keep Out of reach of children.

If swallowed, get medical help or contact a Poison Control Center right away.

Directions

- Take a palmful (5grams) of product in one hand.
- Spread on both hands and rub into skin until dry (approximately 1 to 2 minutes).

Other information

- Do not store above 86℉(30℃)
- May discolor some fabrics
- Harmful to wood finishes and plastics

Inactive ingredients

Water, Carbomer, Glycerin, 2-Amino-2-methyl-1-propanol, Fragrance.